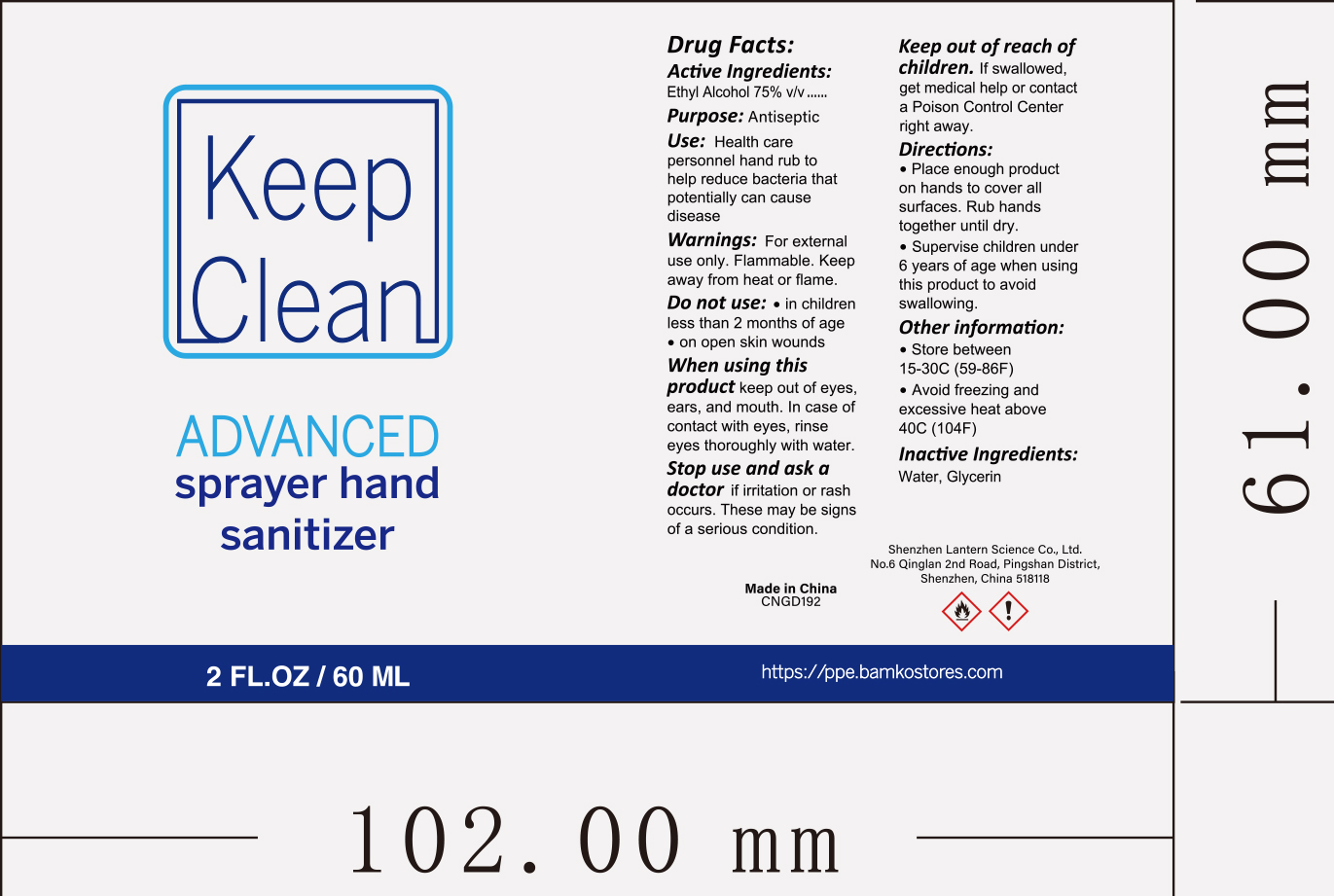 DRUG LABEL: Keep Clean advanced sprayer hand sanitizer 60ml
NDC: 54860-339 | Form: SPRAY
Manufacturer: Shenzhen Lantern Scicence Co.,Ltd.
Category: otc | Type: HUMAN OTC DRUG LABEL
Date: 20201027

ACTIVE INGREDIENTS: ALCOHOL 75 mL/100 mL
INACTIVE INGREDIENTS: WATER 23.55 mL/100 mL; GLYCERIN 1.45 mL/100 mL

Keep Clean advanced sprayer hand sanitizer 60ml

Active Ingredient

Active Ingredient Purpose

Ethyl Alcohol 75%（V/V） Antiseptic

keep out of reach of children

If swallowed,get medical help or contact a Poison Control Center right away.

DOSAGE AND ADMINISTRATION

Recommended for repeated use.

use anywhere without water.

Warning

For external use only,Flammable,Keep away from heat or flame.

WARNINGS AND PRECAUTIONS

For external use only.

Flammable, keep away from heat and flame.

STOP USE

Discontinue if skin becomes irritated and ask a doctor .

Keep out of reach of children. In case of accidental ingestion, seek professional assistance or contact a poson control center immediately.

Inactive ingredients

Water,Glycerin.

Directions

place enough product on hands to cover all surfaces,Rub hands together until dry.Supervise children under 6 years of age when using this product to avoid swallowing.

When using this product

keep out of eyes. In case of contact with eyes, flush thoroughly with water.

Do not inhale or ingest.

Avoid contact with broken skin.

Other information

Do not store above 105F.

May discolor some fabrics.

Harmful to wood finishes and plastics.

When using this product

Keep out of eyes,ears,and mouth.In case of contact with eyes.rinse eyes thoroughly with water.

Purpose

Antiseptic

Stop use and ask a doctor

if irritation or rash occurs,these may be signs of a serious condition.

Use

Health care personel hand rub to help reduce bacteria that potentially can cause disease.

Other information

Store between 15-30C(59-86F).Avoid freezing or excessive heat above 40C(104F).

Do not use

in children less than 2 months of age

on open skin wounds.